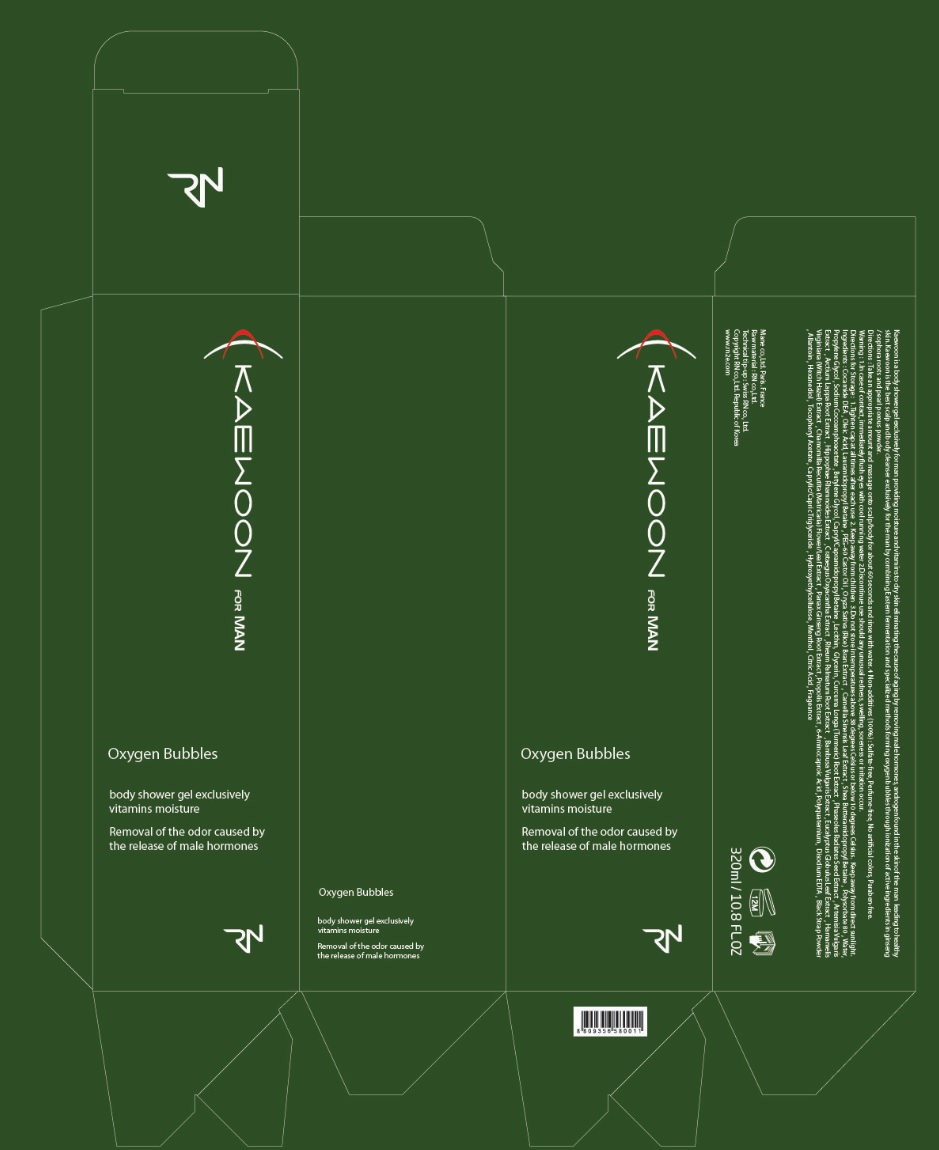 DRUG LABEL: KAEWOON FOR MEN
NDC: 71237-003 | Form: GEL
Manufacturer: RNCARE
Category: otc | Type: HUMAN OTC DRUG LABEL
Date: 20211004

ACTIVE INGREDIENTS: HYALURONIC ACID 20 mg/1 mL; ALLANTOIN 2 mg/1 mL
INACTIVE INGREDIENTS: WATER; POLYQUATERNIUM-10 (1000 MPA.S AT 2%); HYDROXYETHYL CELLULOSE (100 MPA.S AT 2%); MENTHOL, UNSPECIFIED FORM; LAURYL GLUCOSIDE; POLYSORBATE 85; 1,2-HEXANEDIOL; MEDIUM-CHAIN TRIGLYCERIDES; RICE BRAN; TURMERIC; MUNG BEAN; ARCTIUM LAPPA ROOT; HIPPOPHAE RHAMNOIDES SEED; RHEUM PALMATUM ROOT; BAMBUSA VULGARIS WHOLE; HAMAMELIS VIRGINIANA LEAF WATER; MATRICARIA CHAMOMILLA ROOT; SAPINDUS MUKOROSSI FRUIT; EDETATE DISODIUM ANHYDROUS; BUTYLENE GLYCOL; LAURAMIDOPROPYL BETAINE; SODIUM COCOAMPHOACETATE

71237-003_V2

ACTIVE INGREDIENT

HYALURONIC ACID 2%

Allantoin 0.2%

PURPOSE

Skin Protectant

INDICATIONS AND USAGE

Body Cleansing

DOSAGE AND ADMINISTRATION

Take an appropriate amount and massage onto body for about 60 seconds and rinse with water

WARNINGS

In case of eye contact, immediately rinse with water

Stop use if unusual redness, swelling, soreness or irritation occur

Keep out of reach of children

INACTIVE INGREDIENT

Water, Polyquaternium-10 , Hydroxyethylcellulose , Black Strap Powder , Oleic Acid , Menthol , Lauryl Glucoside , Polysorbate 85 , 1,2-Hexanediol , Caprylic/Capric Triglyceride , Oryza Sativa (Rice) Bran Extract , Curcuma Longa (Turmeric Root) Extract, Vigna Radiata Seed Extract , Artemisia Princeps Extract , Arctium Lappa Root Extract , Hippophae Rhamnoides Extract , Hawthorn Crataegus Cuneata Extract Rheum Palmatum Root Extract , Bambusa Vulgaris Extract, Hamamelis Virginiana (Witch Hazel) Extract , Chamomilla Recutita (Matricaria) Extract , Panax Ginseng Root Extract , Propolis Extract , Sapindus Mukurossi Fruit Extract , Disodium EDTA , Diglycerin , Hydrolyzed Collagen , Butylene Glycol , Lauramidopropyl Betaine , Shea Butteramidopropyl Betaine , Capryl/Capramidopropyl Betaine , Sodium Cocoamphoacetate , Fragrance